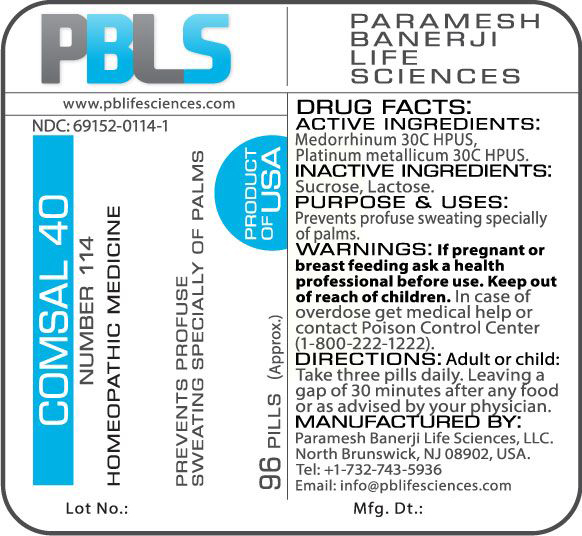 DRUG LABEL: Comsal 40 (Number 114)
NDC: 69152-0114 | Form: PELLET
Manufacturer: Paramesh Banerji Life Sciences LLC
Category: homeopathic | Type: HUMAN OTC DRUG LABEL
Date: 20170601

ACTIVE INGREDIENTS: PLATINUM 30 [hp_C]/1 1; GONORRHEAL URETHRAL SECRETION HUMAN 30 [hp_C]/1 1
INACTIVE INGREDIENTS: LACTOSE; SUCROSE

DRUG FACTS: Active Ingredients

Medorrhinum 30C HPUS, Platinum metallicum 30C HPUS

Inactive Ingredients

Sucrose, Lactose

Purpose

Prevents profuse sweating specially of palms

Uses

Prevents profuse sweating specially of palms

Warnings

If pregnant or breast feeding ask a health professional before use.

Keep out of reach of children. In case of overdose, get medical help or contact a Poison Control Center (1-800-222-1222) right away.

Direction

Adult or child: Take three pills daily. Leaving a gap of 30 minutes after any food or as advised by your physician.

Manufactured by

Paramesh Banerji Life Sciences, LLC

220 North Center Drive

North Brunswick, NJ 08902, USA

Product of USA

Tel: +1-732-743-5936

Principal Display Panel

NDC: 69152-0114-1

Comsal 40

Number 114

Homeopathic Medicine

Prevents profuse sweating specially of palms

96 Pills (Approx.)

Product of USA